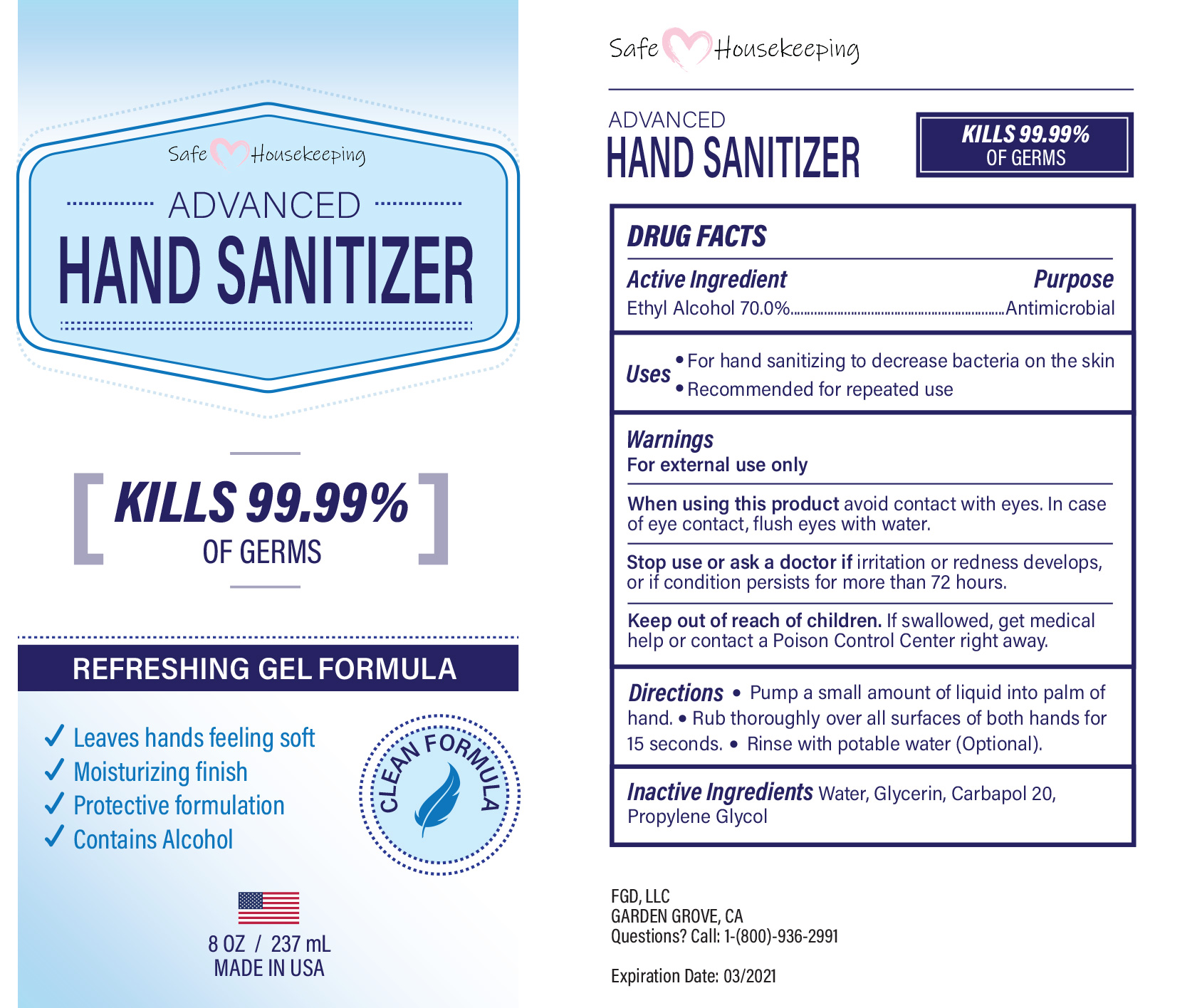 DRUG LABEL: Safe Housekeeping Advanced Hand Sanitizer
NDC: 73787-101 | Form: GEL
Manufacturer: FGD, LLC
Category: otc | Type: HUMAN OTC DRUG LABEL
Date: 20210106

ACTIVE INGREDIENTS: ALCOHOL 165.9 g/237 mL
INACTIVE INGREDIENTS: WATER; PROPYLENE GLYCOL; GLYCERIN

Safe Housekeeping Advanced Hand Sanitizer

Active ingredient

Ethyl Alcohol (70%)

Purpose

Antimicrobial

Uses

- For hand sanitizing to decrease bacteria on the skin

- Recommended for repeated use

Warnings

For external use only

- When using this product avoid contact with eyes. In case of eye contact, flush eyes with water.

Stop use or ask a doctor if irritation or redness develops, or if condition persists for more than 72 hours.

Keep out of reach of children

If swallowed, get medical help or contact a Poison Control Center right away.

Directions

Pump a small amount of liquid into palm of hand.

Rub thoroughly over all surfaces of both hands for 15 seconds.

Rinse with ç water.

Inactive ingredients

Water, Glycerin, Carbapol 20, Propylene Glycol